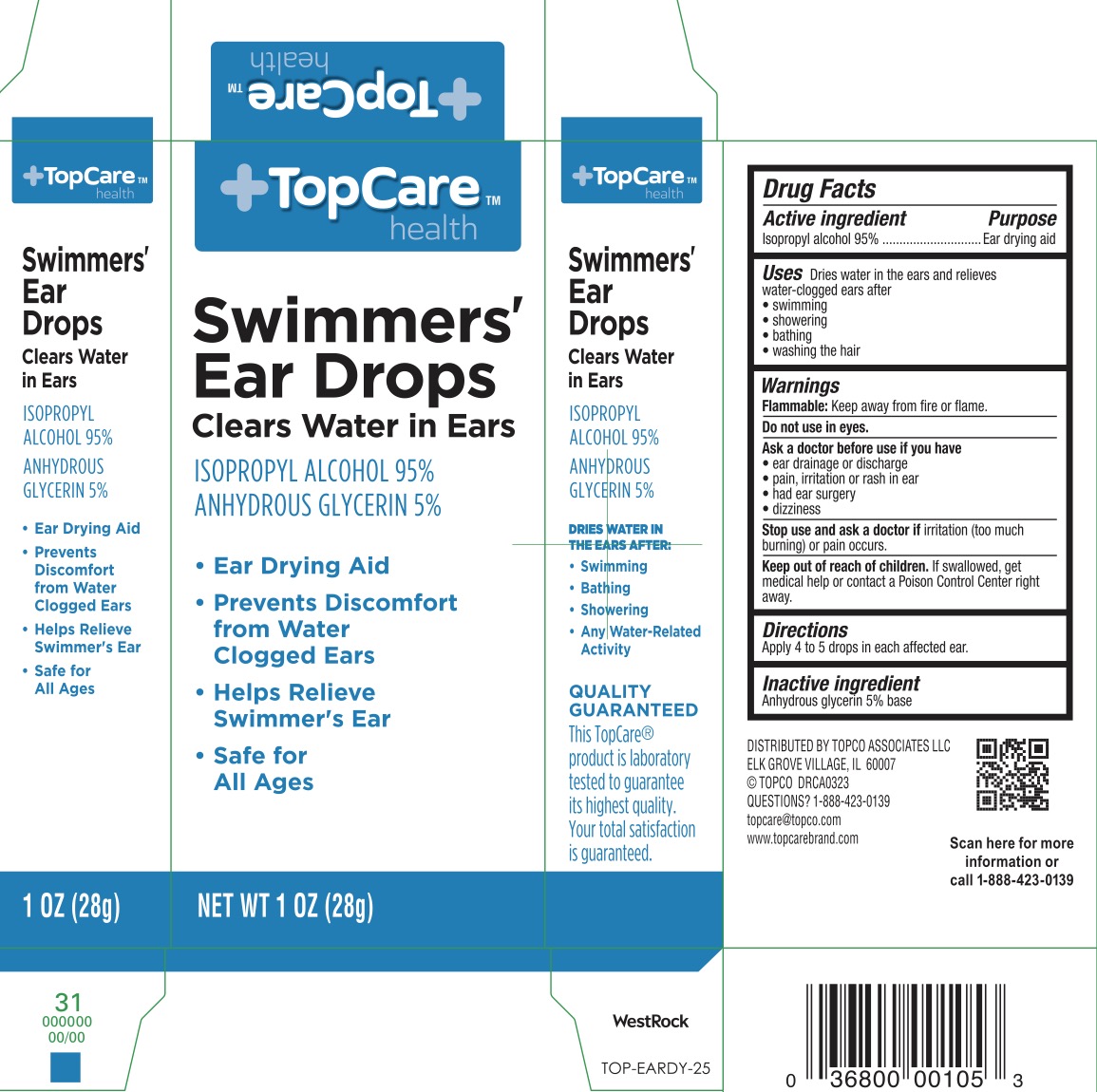 DRUG LABEL: Topcare Swimmers Ear Drops
NDC: 76162-107 | Form: LIQUID
Manufacturer: Topco Associates LLC
Category: otc | Type: HUMAN OTC DRUG LABEL
Date: 20240126

ACTIVE INGREDIENTS: ISOPROPYL ALCOHOL 95 mL/100 g
INACTIVE INGREDIENTS: GLYCERIN

TopCare Swimmers' Ear Drops

ACTIVE INGREDIENT

Isopropyl Alcohol 95%

PURPOSE

Ear drying aid.

INDICATIONS AND USAGE

Dries water in the ears and relieves water-clogged ears after

- swimming
- showering
- bathing
- washing the hair

WARNINGS

Flammable: Keep away from fire or flame.

Do not use in eyes.

Ask a doctor before use if you have

- ear drainage or discharge
- pain, irritation or rash in ear
- had ear surgery
- dizziness

Stop us and ask a doctor if irritation (too much burning) or pain occurs

KEEP OUT OF REACH OF CHILDREN

If swallowed, get medical help or contact a Poison Control Center fight away.

DOSAGE AND ADMINISTRATION

Apply 4 to 5 drops in each affected ear.

INACTIVE INGREDIENT

Anhydrous glycerin 5% base